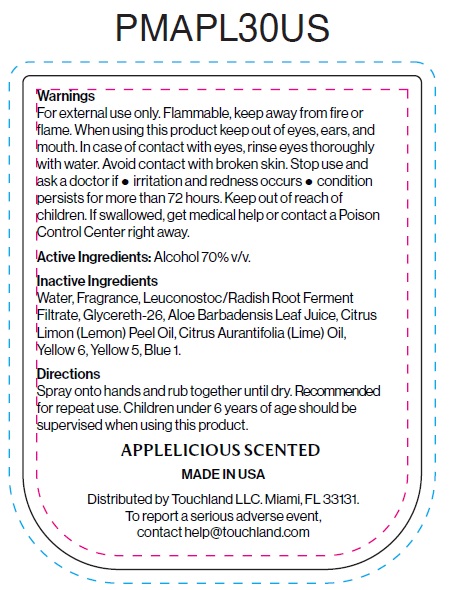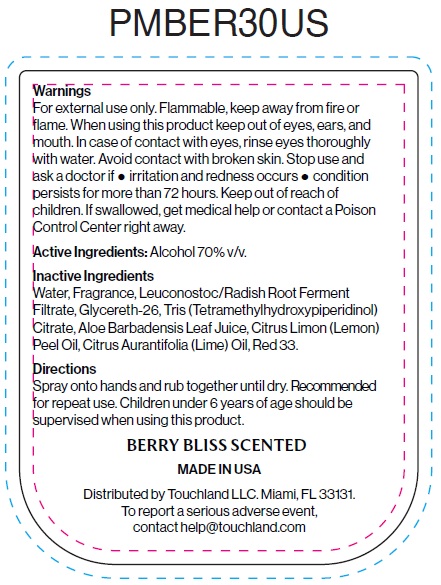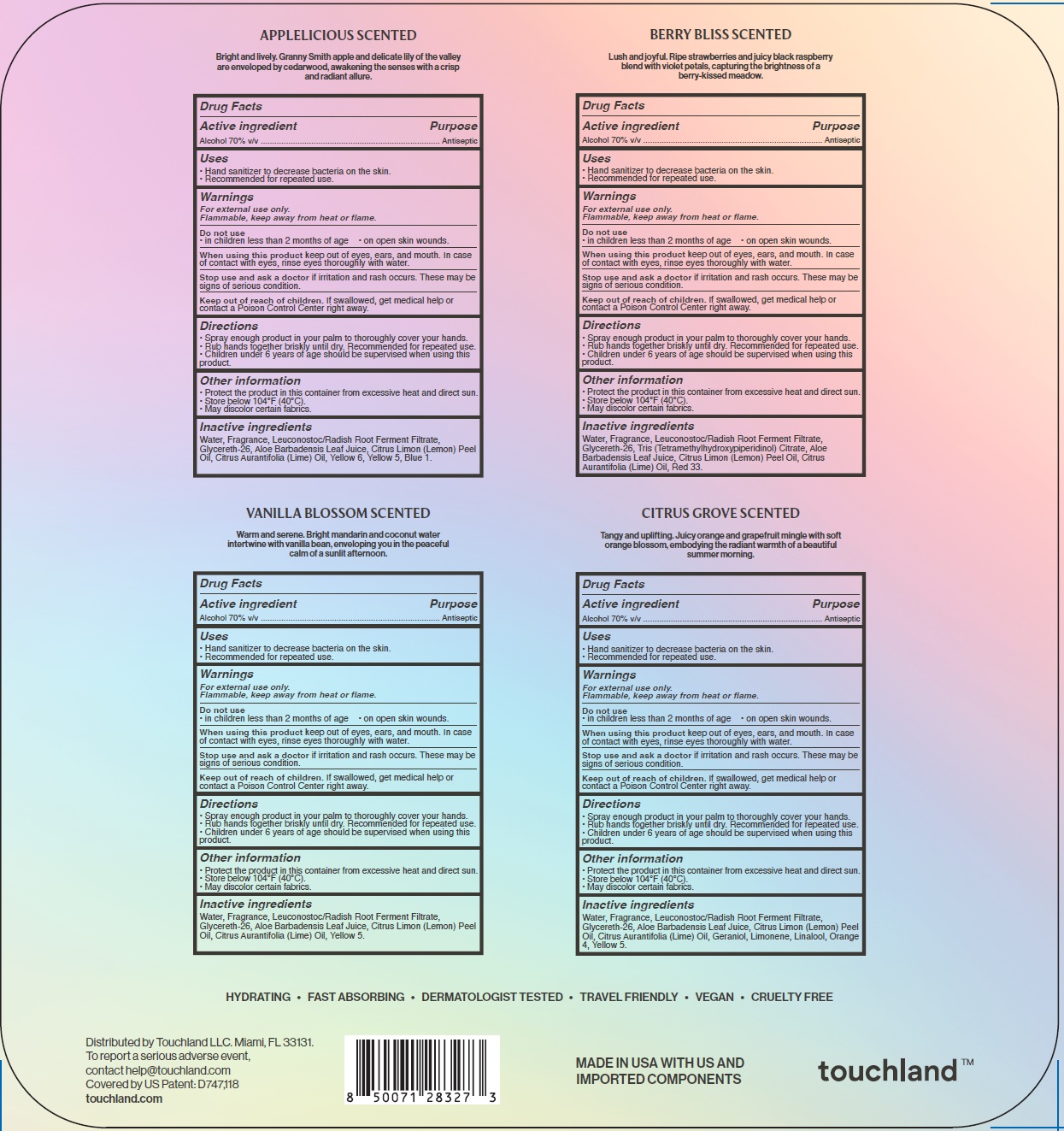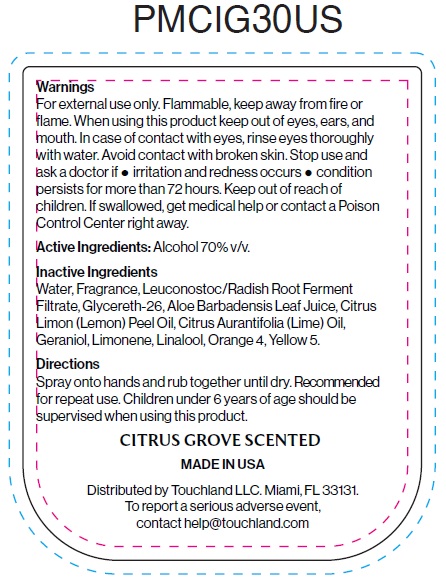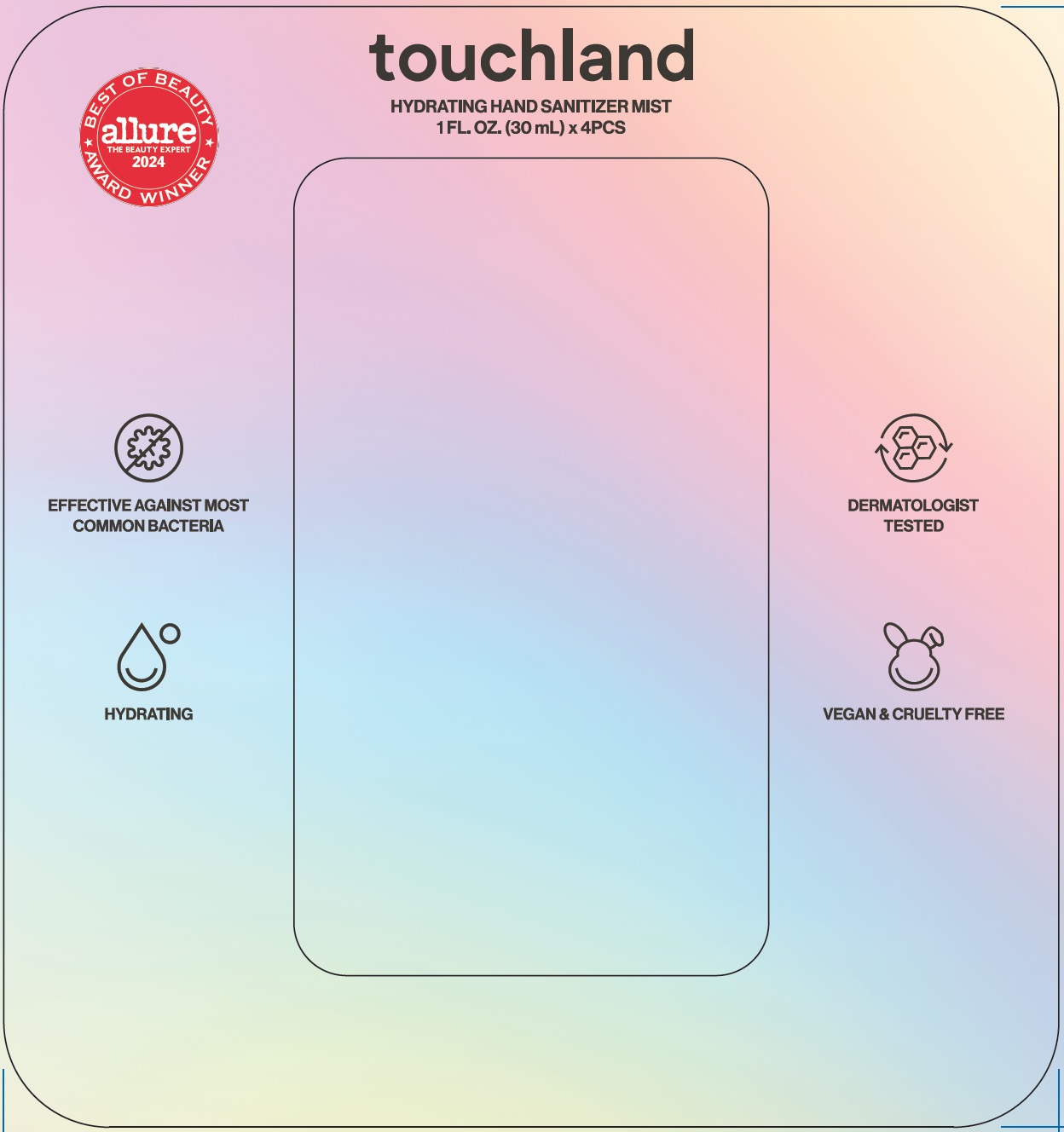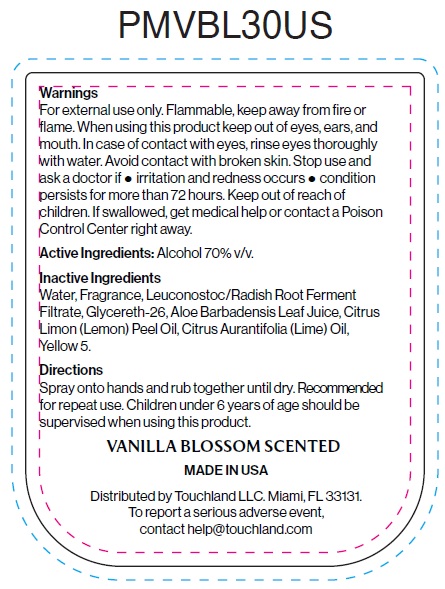 DRUG LABEL: Touchland Hydrating Hand Sanitizer Mist
NDC: 72033-154 | Form: KIT | Route: TOPICAL
Manufacturer: TOUCHLAND LLC
Category: otc | Type: HUMAN OTC DRUG LABEL
Date: 20251014

ACTIVE INGREDIENTS: ALCOHOL 70 mL/100 mL; ALCOHOL 70 mL/100 mL; ALCOHOL 70 mL/100 mL; ALCOHOL 70 mL/100 mL
INACTIVE INGREDIENTS: WATER; LEUCONOSTOC/RADISH ROOT FERMENT FILTRATE; GLYCERETH-26; ALOE VERA LEAF JUICE; LEMON OIL, COLD PRESSED; LIME OIL, COLD PRESSED; FD&C YELLOW NO. 6; FD&C YELLOW NO. 5; FD&C BLUE NO. 1; WATER; LEUCONOSTOC/RADISH ROOT FERMENT FILTRATE; GLYCERETH-26; TRIS(TETRAMETHYLHYDROXYPIPERIDINOL) CITRATE; ALOE VERA LEAF JUICE; LEMON OIL, COLD PRESSED; LIME OIL, COLD PRESSED; D&C RED NO. 33; WATER; LEUCONOSTOC/RADISH ROOT FERMENT FILTRATE; GLYCERETH-26; ALOE VERA LEAF JUICE; LEMON OIL, COLD PRESSED; LIME OIL, COLD PRESSED; FD&C YELLOW NO. 5; WATER; LEUCONOSTOC/RADISH ROOT FERMENT FILTRATE; GLYCERETH-26; ALOE VERA LEAF JUICE; LEMON OIL, COLD PRESSED; LIME OIL, COLD PRESSED; GERANIOL; LIMONENE, (+)-; LINALOOL, (+/-)-; D&C ORANGE NO. 4; FD&C YELLOW NO. 5

Touchland Hydrating Hand Sanitizer Mist

Active ingredient

Alcohol 70% v/v

Purpose

Antiseptic

Uses

- Hand sanitizer to decrease bacteria on the skin.
- Recommended for repeated use.

Warnings

For external use only.

Flammable, keep away from heat or flame.

Do not use

- in children less than 2 months of age
- on open skin wounds.

When using this product

keep out of eyes, ears and mouth. In case of contact with eyes, rinse eyes thoroughly with water.

Stop use and ask a doctor

if irritation and rash occurs. These may be sings of serious condition.

Keep out of reach of children.

If swallowed, get medical help or contact a Poison Control Center right away.

Directions

- Spray enough product in your palm to thoroughly cover your hands.
- Rub hands together briskly until dry. Recommended for repeated use.
- Children under 6 years of age should be supervised when using this product.

Other information

- Protect the product in this container from excessive heat and direct sun.
- Store below 104°F (40°C).
- May discolor certain fabrics.

Inactive ingredients

Water, Fragrance, Leuconostoc/Radish Root Ferment Filtrate, Glycereth-26, Aloe Barbadensis Leaf Juice, Citrus Limon (Lemon) Peel Oil, Citrus Aurantifolia (Lime) Oil, Yellow 6, Yellow 5, Blue 1.

Active ingredient

Alcohol 70% v/v

Purpose

Antiseptic

Uses

- Hand sanitizer to decrease bacteria on the skin.
- Recommended for repeated use.

Warnings

For external use only.

Flammable, keep away from heat or flame.

Do not use

- in children less than 2 months of age
- on open skin wounds.

When using this product

keep out of eyes, ears and mouth. In case of contact with eyes, rinse eyes thoroughly with water.

Stop use and ask a doctor

if irritation and rash occurs. These may be sings of serious condition.

Keep out of reach of children.

If swallowed, get medical help or contact a Poison Control Center right away.

Directions

- Spray enough product in your palm to thoroughly cover your hands.
- Rub hands together briskly until dry. Recommended for repeated use.
- Children under 6 years of age should be supervised when using this product.

Other information

- Protect the product in this container from excessive heat and direct sun.
- Store below 104°F (40°C).
- May discolor certain fabrics.

Inactive ingredients

Water, Fragrance, Leuconostoc/Radish Root Ferment Filtrate, Glycereth-26, Tris (Tetramethylhydroxyperidinol) Citrate, Aloe Barbadensis Leaf Juice, Citrus Limon (Lemon) Peel Oil, Citrus Aurantifolia (Lime) Oil, Red 33.

Active ingredient

Alcohol 70% v/v

Purpose

Antiseptic

Uses

- Hand sanitizer to decrease bacteria on the skin.
- Recommended for repeated use.

Warnings

For external use only.

Flammable, keep away from heat or flame.

Do not use

- in children less than 2 months of age
- on open skin wounds.

When using this product

keep out of eyes, ears and mouth. In case of contact with eyes, rinse eyes thoroughly with water.

Stop use and ask a doctor

if irritation and rash occurs. These may be sings of serious condition.

Keep out of reach of children.

If swallowed, get medical help or contact a Poison Control Center right away.

Directions

- Spray enough product in your palm to thoroughly cover your hands.
- Rub hands together briskly until dry. Recommended for repeated use.
- Children under 6 years of age should be supervised when using this product.

Other information

- Protect the product in this container from excessive heat and direct sun.
- Store below 104°F (40°C).
- May discolor certain fabrics.

Inactive ingredients

Water, Fragrance, Leuconostoc/Radish Root Ferment Filtrate, Glycereth-26, Aloe Barbadensis Leaf Juice, Citrus Limon (Lemon) Peel Oil, Citrus Aurantifolia (Lime) Oil, Yellow 5.

Active ingredient

Alcohol 70% v/v

Purpose

Antiseptic

Uses

- Hand sanitizer to decrease bacteria on the skin.
- Recommended for repeated use.

Warnings

For external use only.

Flammable, keep away from heat or flame.

Do not use

- in children less than 2 months of age
- on open skin wounds.

When using this product

keep out of eyes, ears and mouth. In case of contact with eyes, rinse eyes thoroughly with water.

Stop use and ask a doctor

if irritation and rash occurs. These may be sings of serious condition.

Keep out of reach of children.

If swallowed, get medical help or contact a Poison Control Center right away.

Directions

- Spray enough product in your palm to thoroughly cover your hands.
- Rub hands together briskly until dry. Recommended for repeated use.
- Children under 6 years of age should be supervised when using this product.

Other information

- Protect the product in this container from excessive heat and direct sun.
- Store below 104°F (40°C).
- May discolor certain fabrics.

Inactive ingredients

Water, Fragrance, Leuconostoc/Radish Root Ferment Filtrate, Glycereth-26, Aloe Barbadensis Leaf Juice, Citrus Limon (Lemon) Peel Oil, Citrus Aurantifolia (Lime) Oil, Geraniol, Limonene, Linalool, Orange 4, Yellow 5.